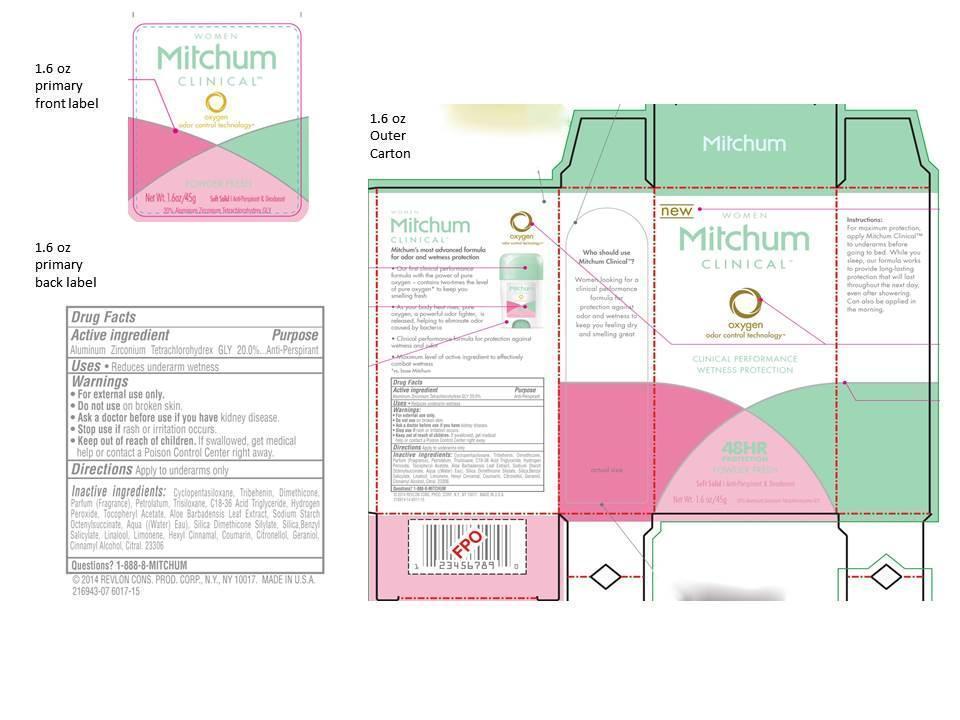 DRUG LABEL: Womens Mitchum Clinical Antiperspirant Deodorant
NDC: 10967-595 | Form: CREAM
Manufacturer: Revlon Consumer Products Corp
Category: otc | Type: HUMAN OTC DRUG LABEL
Date: 20140217

ACTIVE INGREDIENTS: ALUMINUM ZIRCONIUM TETRACHLOROHYDREX GLY 0.20 g/1 g
INACTIVE INGREDIENTS: CYCLOMETHICONE 5; TRIBEHENIN; DIMETHICONE; PETROLATUM; TRISILOXANE; C18-36 ACID TRIGLYCERIDE; HYDROGEN PEROXIDE; .ALPHA.-TOCOPHEROL ACETATE; ALOE VERA LEAF; WATER; SILICON DIOXIDE; BENZYL SALICYLATE; LINALOOL, (+/-)-; LIMONENE, (+/-)-; .ALPHA.-HEXYLCINNAMALDEHYDE; COUMARIN; .BETA.-CITRONELLOL, (R)-; GERANIOL; CINNAMYL ALCOHOL; CITRAL

Womens Mitchum Clinical Antiperspirant Deodorant Soft Solid (Powder Fresh)- 1.6 oz.

Drug Facts Active Ingredient

Aluminum zirconium tetrachlorohydrex gly 20%

Purpose

Antiperspirant

Use

- Reduces underarm wetness

Warnings:

For external use only.

Do not use on broken skin

Ask a doctor before use if you have kidney disease

Stop use if rash or irriation occurs

Keep out of reach of children.

If swallowed, get medical help or contact a Poison Control Center right away.

Directions

Apply to underarms only.

Inactive Ingredients

cyclopentasiloxane, tribehenin, dimethicone, parfum (fragrance), petrolatum, trisiloxane, c18-36 acid triglyceride, hydrogen peroxide, tocopheryl acetate, aloe barbadensis leaf extract, sodium starch octenylsuccinate, aqua((water) eau), silica dimethicone silylate, silica, benzyl salicylate, linalool, limonene, hexyl cinnamal, coumarin, citronellol, geraniol, cinnamyl alcohol, citral

Questions

1-888-8-MITCHUM